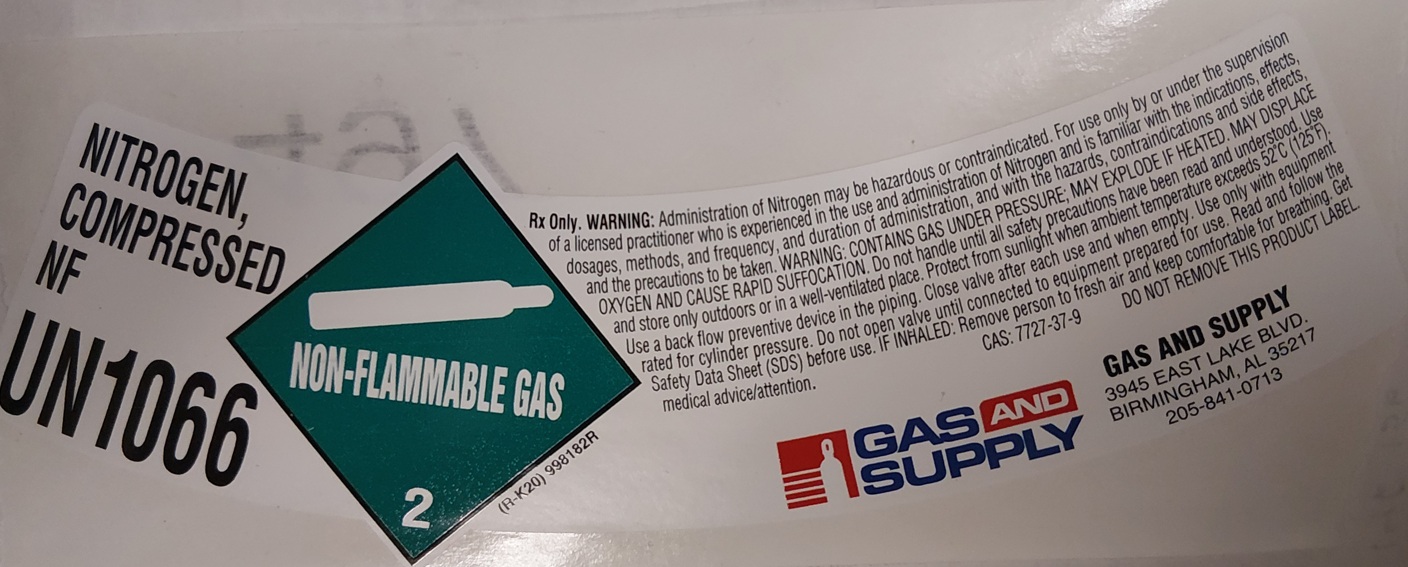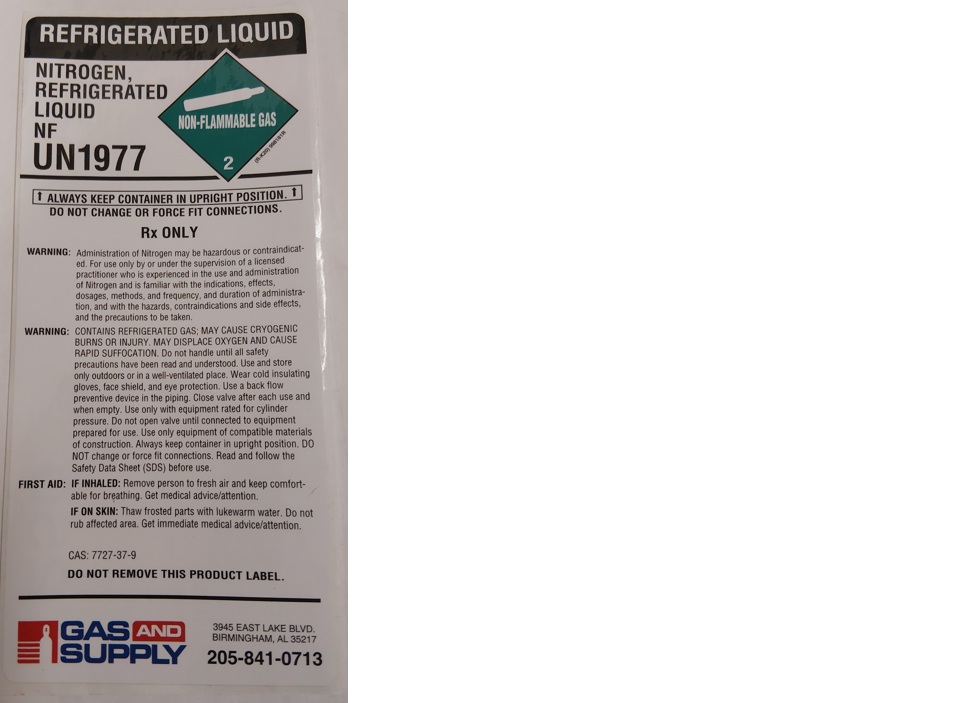 DRUG LABEL: Nitrogen
NDC: 76349-002 | Form: GAS
Manufacturer: Southern Gas & Supply LLC
Category: prescription | Type: HUMAN PRESCRIPTION DRUG LABEL
Date: 20251208

ACTIVE INGREDIENTS: NITROGEN 995 mL/1 L

Nitrogen

PACKAGE LABEL

NITROGEN, COMPRESSED NF

UN1066

Rx Only. WARNING: Administration of Nitrogen may be hazardous or contraindicated. For use only by or under the supervision of a licensed practitioner who is experienced in the use and administration of Nitrogen and is familiar with the indications, effects, dosages, methods, and frequency, and duration of administration, and with the hazards, contraindications and side effects, and the precautions to be taken. WARNING: CONTAINS GAS UNDER PRESSURE; MAY EXPLODE IF HEATED. MAY DISPLACE OXYGEN AND CAUSE RAPID SUFFOCATION. Do not handle until all safety precautions have been read and understood. Use and store only outdoors or in a well-ventilated place. Protect from sunlight when ambient temperature exceeds 52 C (125 F). Use a back flow preventive device in the piping. Close valve after each use and when empty. Use only with equipment rated for cylinder pressure. Do not open valve until connected to equipment prepared for use. Read and follow the Safety Data Sheet (SDS) before use. IF INHALED: Remove person to fresh air and keep comfortable for breathing. Get medical advice/attention.

CAS: 7727-37-9 DO NOT REMOVE THIS PRODUCT LABEL.

GAS AND SUPPLY

GAS AND SUPPLY

3945 EAST LAKE BLVD.

BIRMINGHAM, AL 35217

205-841-0713

PACKAGE LABEL

REFRIGERATED LIQUID

NITROGEN, REFRIGERATED LIQUID NF

UN1977

ALWAYS KEEP CONTAINER IN UPRIGHT POSITION.

DO NOT CHANGE OR FORCE FIT CONNECTIONS.

Rx ONLY

WARNING: Administration of Nitrogen may be hazardous or contraindicated. For use only by or under the supervision of a licensed practitioner who is experienced in the use and administration of Nitrogen and is familiar with the indications, effects, dosages, methods, and frequency, and duration of administration, and with the hazards, contraindications and side effects, and the precautions to be taken.

WARNING: CONTAINS REFRIGERATED GAS; MAY CAUSE CRYOGENIC BURNS OR INJURY. MAY DISPLACE OXYGEN AND CAUSE RAPID SUFFOCATION. Do not handle until all safety precautions have been read and understood. Use and store only outdoors or in a well-ventilated place. Wear cold insulating gloves, face shield, and eye protection. Use a back flow preventive device in the piping. Close valve after each use and when empty. Use only with equipment rated for cylinder pressure. Do not open valve until connected to equipment prepared for use. Use only equipment of compatible materials of construction. Always keep container in upright position. DO NOT change or force fit connections. Read and follow the Safety Data Sheet (SDS) before use.

FIRST AID: IF INHALED: Remove person to fresh air and keep comfortable for breathing. Get medical advice/attention.

IF ON SKIN: Thaw frosted parts with lukewarm water. Do not rub affected area. Get immediate medical advice/attention.

CAS: 7727-37-9

DO NOT REMOVE THIS PRODUCT LABEL.

GAS AND SUPPLY

3945 EAST LAKE BLVD.

BIRMINGHAM, AL 35217

205-841-0713